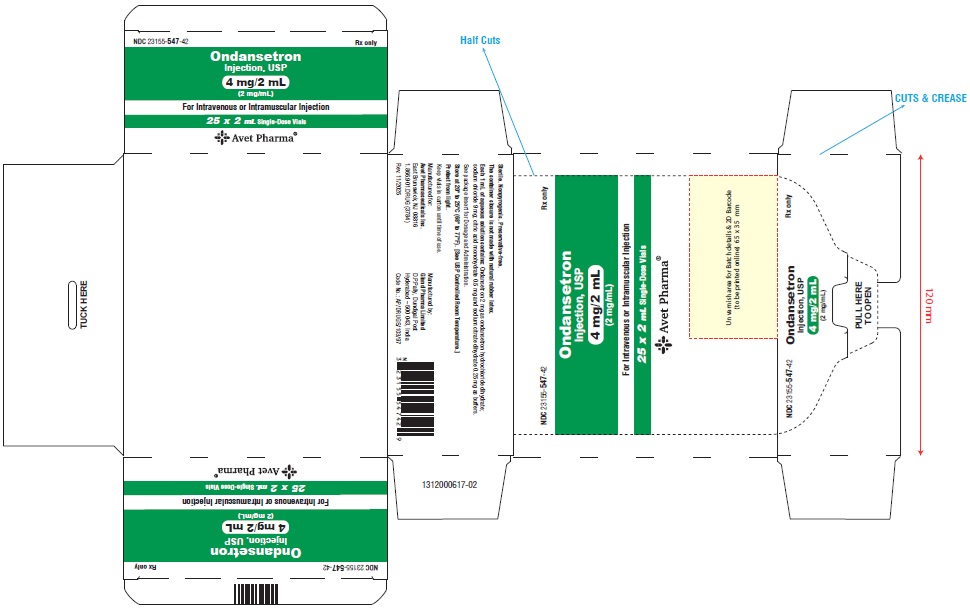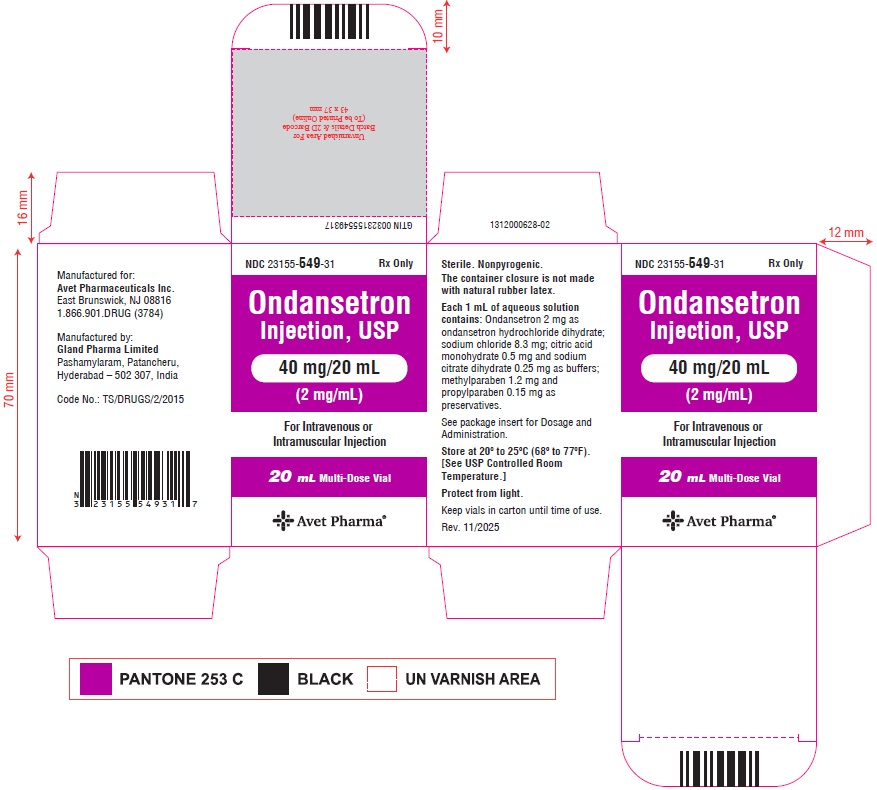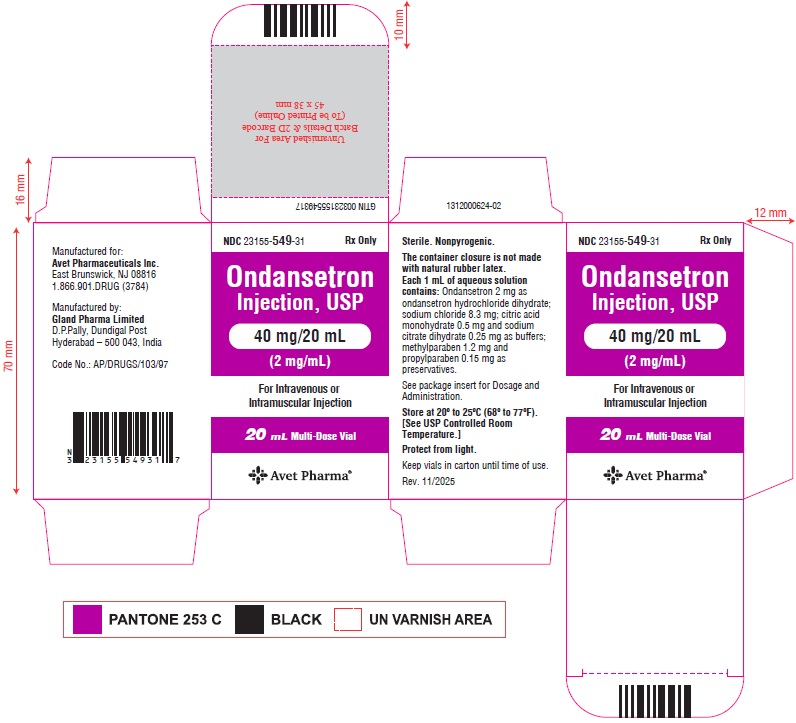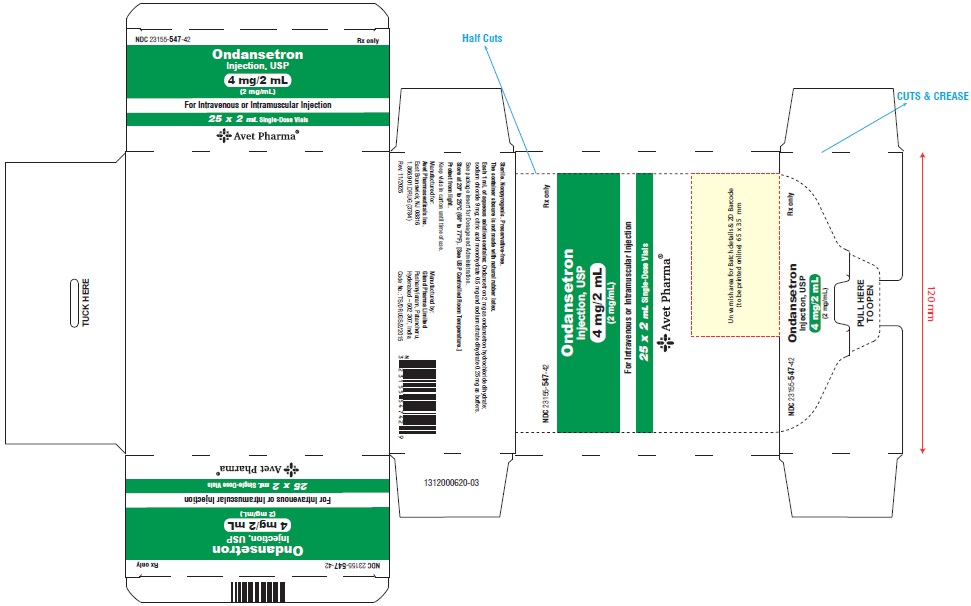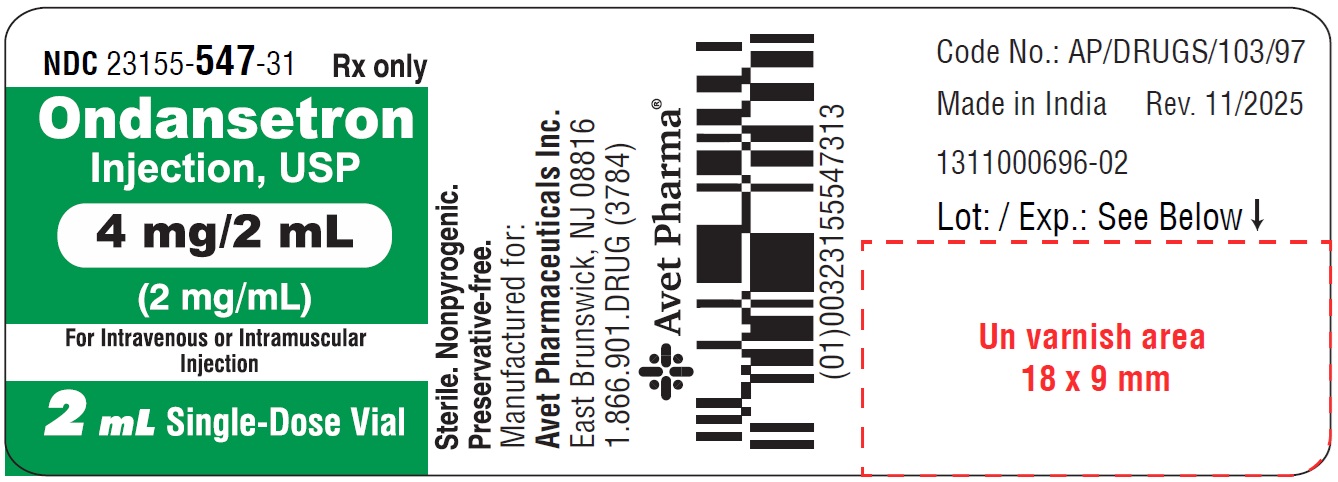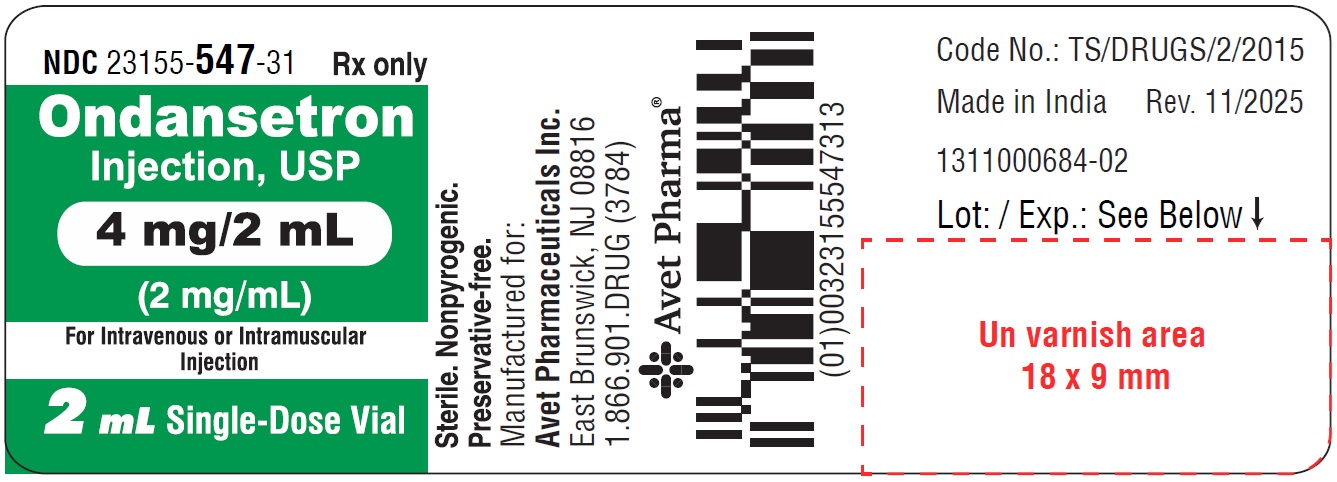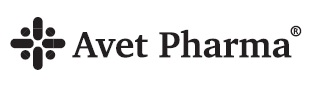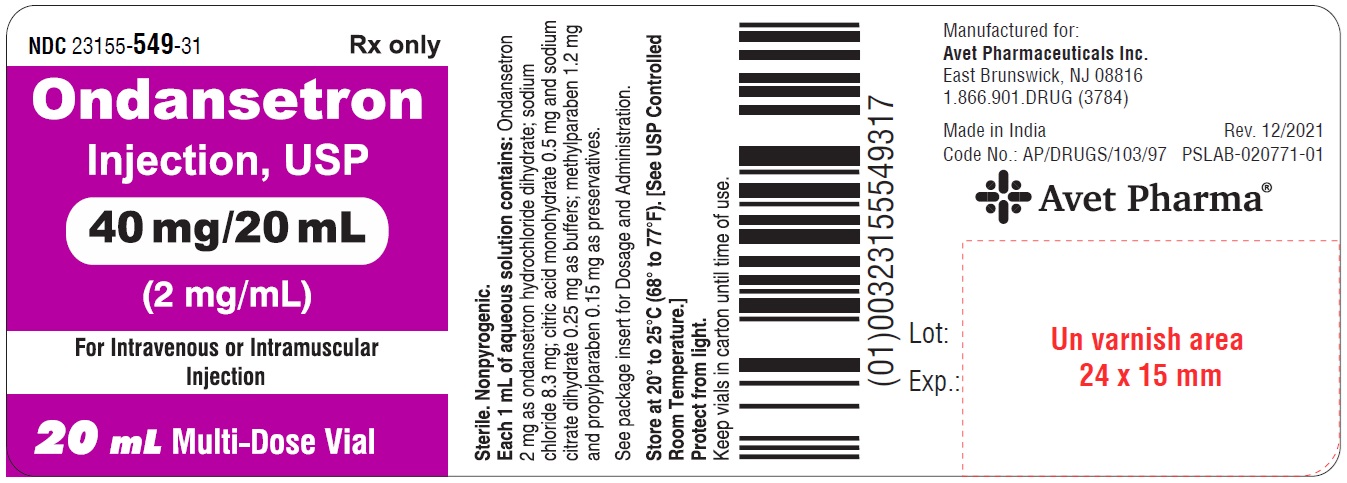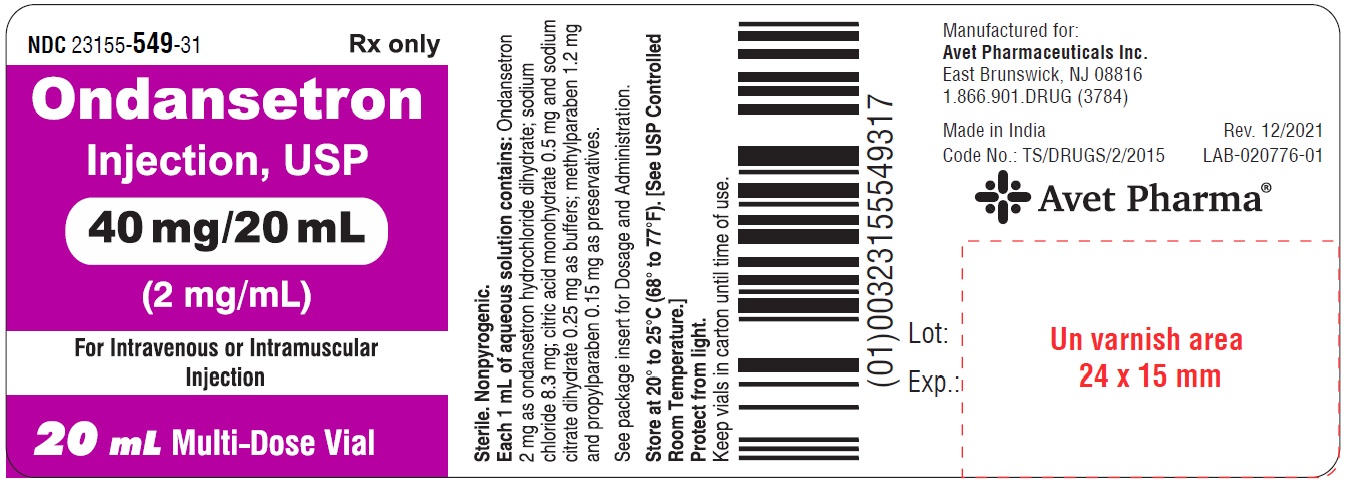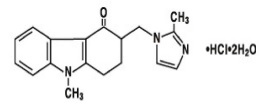 DRUG LABEL: ONDANSETRON
NDC: 23155-547 | Form: INJECTION
Manufacturer: Heritage Pharmaceuticals Inc. d/b/a Avet Pharmaceuticals Inc.
Category: prescription | Type: Human Prescription Drug Label
Date: 20260213

ACTIVE INGREDIENTS: ONDANSETRON HYDROCHLORIDE 2 mg/1 mL
INACTIVE INGREDIENTS: SODIUM CHLORIDE 9.0 mg/1 mL; CITRIC ACID MONOHYDRATE 0.5 mg/1 mL; SODIUM CITRATE 0.25 mg/1 mL

HIGHLIGHTS OF PRESCRIBING INFORMATION

These highlights do not include all the information needed to use ONDANSETRON INJECTION safely and effectively. See full prescribing information for ONDANSETRON INJECTION.
ONDANSETRON injection, for intravenous or intramuscular use
Initial U.S. Approval: 1991

1 INDICATIONS AND USAGE

Ondansetron Injection is a 5-HT3 receptor antagonist indicated for the prevention of:

- nausea and vomiting associated with initial and repeat courses of emetogenic cancer chemotherapy. (1.1)
- postoperative nausea and/or vomiting. (1.2)

2 DOSAGE AND ADMINISTRATION

Prevention of Nausea and Vomiting Associated With Initial and Repeat Courses of Emetogenic Cancer Chemotherapy (2.1):

- Dilution of Ondansetron Injection in 50 mL of 5% Dextrose Injection or 0.9% Sodium Chloride Injection is required before administration to adult and pediatric patients.
- Adults and pediatric patients 6 months of age and older: The recommended dosage is 0.15 mg/kg per dose for 3 doses (maximum of 16 mg per dose), infused intravenously over 15 minutes.
- Administer the first dose 30 minutes before the start of chemotherapy and subsequent doses 4 and 8 hours after the first dose.

Prevention of Postoperative Nausea and/or Vomiting (2.2):

- Dilution of Ondansetron Injection is not required before administration to adult and pediatric patients.
- See full prescribing information for the recommended dosage and administration instructions for adult and pediatric patients 1 month of age and older.

Patients With Severe Hepatic Impairment (2.3):

- Do not exceed a total daily dose of 8 mg.

3 DOSAGE FORMS AND STRENGTHS

Ondansetron Injection (2 mg per mL): 2 mL Single-Dose Vial and 20 mL Multi-Dose Vial. (3)

4 CONTRAINDICATIONS

- Patients known to have hypersensitivity (e.g., anaphylaxis) to this product or any of its components. (4)
- Concomitant use of apomorphine. (4, 7.2)

5 WARNINGS AND PRECAUTIONS

- Hypersensitivity Reactions: Hypersensitivity reactions, including anaphylaxis and bronchospasm have been reported in patients who have exhibited hypersensitivity to other selective 5-HT3 receptor antagonists. (5.1)
- QT Prolongation and Torsade de Pointes: QT prolongation occurs in a dose-dependent manner. Cases of Torsade de Pointes have been reported. Avoid ondansetron injection in patients with congenital long QT syndrome. (5.2)
- Serotonin Syndrome: Serotonin syndrome has been reported with 5-HT3 receptor agonists alone but particularly with concomitant use of serotonergic drugs. (5.3)
- Myocardial Ischemia: Do not exceed the recommended infusion rate and monitor patients during and after administration. (2.1, 2.2, 5.4)
- Masking of Progressive Ileus and/or Gastric Distension Following Abdominal Surgery or Chemotherapy-Induced Nausea and Vomiting: Monitor for decreased bowel activity, particularly in patients with risk factors for gastrointestinal obstruction. (5.5)

6 ADVERSE REACTIONS

Chemotherapy-Induced Nausea and Vomiting:

- The most common adverse reactions (≥7%) in adults are diarrhea, headache, and fever. (6.1)

Postoperative Nausea and/or Vomiting:

- The most common adverse reaction (≥10%) which occurs at a higher frequency compared with placebo in adults is headache. (6.1)
- The most common adverse reaction (≥2%) which occurs at a higher frequency compared with placebo in pediatric patients aged 1 to 24 months is diarrhea. (6.1)

To report SUSPECTED ADVERSE REACTIONS, contact Avet Pharmaceuticals Inc. at 1-866-901-DRUG (3784) or FDA at 1-800-FDA-1088 or www.fda.gov/medwatch.

FULL PRESCRIBING INFORMATION

1 INDICATIONS AND USAGE

1.1 Prevention of Nausea and Vomiting Associated With Initial and Repeat Courses of Emetogenic Cancer Chemotherapy

Ondansetron Injection is indicated for the prevention of nausea and vomiting associated with initial and repeat courses of emetogenic cancer chemotherapy, including high-dose cisplatin.

Ondansetron Injection is approved for patients aged 6 months and older.

1.2 Prevention of Postoperative Nausea and/or Vomiting

Ondansetron Injection is indicated for the prevention of postoperative nausea and/or vomiting. As with other antiemetics, routine prophylaxis is not recommended for patients in whom there is little expectation that nausea and/or vomiting will occur postoperatively. In patients in whom nausea and/or vomiting must be avoided postoperatively, Ondansetron Injection is recommended even when the incidence of postoperative nausea and/or vomiting is low. For patients who do not receive prophylactic Ondansetron Injection and experience nausea and/or vomiting postoperatively, Ondansetron Injection may be given to prevent further episodes.

Ondansetron Injection is approved for patients aged 1 month and older.

2 DOSAGE AND ADMINISTRATION

2.1 Prevention of Nausea and Vomiting Associated With Initial and Repeat Courses of Emetogenic Chemotherapy

Important Preparation Instructions

- Dilution of ondansetron injection in 50 mL of 5% Dextrose Injection or 0.9% Sodium Chloride Injection is required before administration to adult and pediatric patients for the prevention of nausea and vomiting associated with emetogenic chemotherapy.

For pediatric patients between 6 months and 1 year of age and/or 10 kg or less: Depending on the fluid needs of the patient, ondansetron injection may be diluted in 10 to 50 mL of 5% Dextrose Injection or 0.9% Sodium Chloride Injection.

- Occasionally, ondansetron precipitates at the stopper/vial interface in vials stored upright. Potency and safety are not affected. If a precipitate is observed, resolubilize by shaking the vial vigorously.
- Do not mix ondansetron injection with solutions for which physical and chemical compatibility has not been established. In particular, this applies to alkaline solutions as a precipitate may form.
- Inspect the diluted ondansetron injection solution for particulate matter and discoloration before administration; discard if present.
- Storage: After dilution, do not use beyond 24 hours. Although ondansetron injection is chemically and physically stable when diluted as recommended, sterile precautions should be observed because diluents generally do not contain preservative.
- Compatibility: Ondansetron injection is compatible and stable at room temperature under normal lighting conditions for 48 hours after dilution with the following intravenous fluids: 0.9% Sodium Chloride Injection, 5% Dextrose Injection, 5% Dextrose and 0.9% Sodium Chloride Injection, 5% Dextrose and 0.45% Sodium Chloride Injection, and 3% Sodium Chloride Injection.

Dosage and Administration
The recommended dosage for adult and pediatric patients 6 months of age and older for prevention of nausea and vomiting associated with emetogenic chemotherapy is 0.15-mg/kg per dose for 3 doses (maximum of 16 mg per dose).
Caution: Dilution of ondansetron injection is required in adult and pediatric patients prior to administration.
Infuse intravenously over 15 minutes beginning 30 minutes before the start of emetogenic chemotherapy and then repeat 4 and 8 hours after the first dose.

2.2 Prevention of Postoperative Nausea and/or Vomiting

Important Preparation Instructions
• Dilution of ondansetron injection is not required before administration to adult and pediatric patients.

• Inspect ondansetron injection visually for particulate matter and discoloration before administration; discard if present.

Dosage and Administration The recommended dose and administration instructions for adult and pediatric patients 1 month of age and older for prevention of postoperative nausea and vomiting are shown in Table 1.
Table 1: Recommended Dose and Administration of Ondansetron Injection for Prevention of Postoperative Nausea and/or Vomiting

Population | Recommended Single Dose | Administration Instructions | Timing of Administration
Adults and pediatric patients older than 12 years of age | 4 mg1 | May be administered intravenously or intramuscularly:; 1. Intravenously: infuse undiluted syringe contents (4 mg) over at least 30 seconds and preferably longer (over 2 to 5 minutes). 2. Intramuscularly: inject undiluted syringe contents (4 mg). | Administer immediately before induction of anesthesia, or postoperatively if the patient did not receive prophylactic antiemetics and experiences nausea and/or vomiting occurring within 2 hours after surgery^2,3
Pediatric patients 1 month to 12 years and more than 40 kg | 4 mg | Infuse intravenously over at least 30 seconds and preferably longer (over 2 to 5 minutes).
Pediatric patients 1 month to 12 years and 40 kg or less | 0.1 mg/kg | Infuse intravenously over at least 30 seconds and preferably longer (over 2 to 5 minutes).

^1. Few patients above 80 kg have been studied.
^2. Administration of a second intravenous dose of 4 mg ondansetron postoperatively in adult patients who received a 4 mg prophylactic dose does not provide additional control of nausea and vomiting [see Clinical Studies (14.3)].
^3. For pediatric patients (1 month to 12 years) prevention of nausea and vomiting was only studied in patients who had not received prophylactic ondansetron.

2.3 Dosage Adjustment for Patients With Hepatic Impairment

In patients with severe hepatic impairment (Child-Pugh score of 10 or greater), a single maximal daily dose of 8 mg infused over 15 minutes beginning 30 minutes before the start of the emetogenic chemotherapy is recommended. There is no experience beyond first-day administration of ondansetron in these patients [see Use in Specific Populations (8.6)].

3 DOSAGE FORMS AND STRENGTHS

Ondansetron Injection, USP 2 mg per mL is a clear, colorless, nonpyrogenic, sterile solution available as a 2 mL Single-Dose Vial and 20 mL Multi-Dose Vial.

4 CONTRAINDICATIONS

Ondansetron injection is contraindicated for patients known to have hypersensitivity (e.g., anaphylaxis) to this product or any of its components. Anaphylactic reactions have been reported in patients taking ondansetron [see Adverse Reactions (6.2)].

The concomitant use of apomorphine with ondansetron is contraindicated based on reports of profound hypotension and loss of consciousness when apomorphine was administered with ondansetron.

5 WARNINGS AND PRECAUTIONS

5.1 Hypersensitivity Reactions

Hypersensitivity reactions, including anaphylaxis and bronchospasm, have been reported in patients who have exhibited hypersensitivity to other selective 5-HT3 receptor antagonists.

5.2 QT Prolongation

Ondansetron prolongs the QT interval in a dose-dependent manner [see Clinical Pharmacology (12.2)]. In addition, postmarketing cases of Torsade de Pointes have been reported in patients using ondansetron. Avoid ondansetron injection in patients with congenital long QT syndrome. Electrocardiogram (ECG) monitoring is recommended in patients with electrolyte abnormalities (e.g., hypokalemia or hypomagnesemia), congestive heart failure, bradyarrhythmias, or patients taking other medicinal products that lead to QT prolongation.

5.3 Serotonin Syndrome

The development of serotonin syndrome has been reported with 5-HT3 receptor antagonists. Most reports have been associated with concomitant use of serotonergic drugs (e.g., selective serotonin reuptake inhibitors (SSRIs), serotonin and norepinephrine reuptake inhibitors (SNRIs), monoamine oxidase inhibitors, mirtazapine, fentanyl, lithium, tramadol, and intravenous methylene blue). Some of the reported cases were fatal. Serotonin syndrome occurring with overdose of ondansetron alone has also been reported. The majority of reports of serotonin syndrome related to 5-HT3 receptor antagonist use occurred in a post-anesthesia care unit or an infusion center.

Symptoms associated with serotonin syndrome may include the following combination of signs and symptoms: mental status changes (e.g., agitation, hallucinations, delirium, and coma), autonomic instability (e.g., tachycardia, labile blood pressure, dizziness, diaphoresis, flushing, hyperthermia), neuromuscular symptoms (e.g., tremor, rigidity, myoclonus, hyperreflexia, incoordination), seizures, with or without gastrointestinal symptoms (e.g., nausea, vomiting, diarrhea). Patients should be monitored for the emergence of serotonin syndrome, especially with concomitant use of ondansetron injection and other serotonergic drugs. If symptoms of serotonin syndrome occur, discontinue ondansetron injection and initiate supportive treatment. Patients should be informed of the increased risk of serotonin syndrome, especially if ondansetron injection is used concomitantly with other serotonergic drugs [see Drug Interactions (7.5), Overdosage (10)].

5.4 Myocardial Ischemia

Myocardial ischemia has been reported in patients treated with ondansetron. In some cases, predominantly during intravenous administration, the symptoms appeared immediately after administration but resolved with prompt treatment. Coronary artery spasm appears to be the most common underlying cause. Therefore, do not exceed the recommended infusion rate of ondansetron injection and monitor patients for signs and symptoms of myocardial ischemia during and after administration [see Dosage and Administration (2.1,2.2) and Adverse Reactions (6.2)].

5.5 Masking of Progressive Ileus and Gastric Distension

The use of ondansetron injection in patients following abdominal surgery or in patients with chemotherapy-induced nausea and vomiting may mask a progressive ileus and gastric distension. Monitor for decreased bowel activity, particularly in patients with risk factors for gastrointestinal obstruction.

Ondansetron injection is not a drug that stimulates gastric or intestinal peristalsis. It should not be used instead of nasogastric suction.

6 ADVERSE REACTIONS

The following clinically significant adverse reactions are described elsewhere in the labeling:
• Hypersensitivity Reactions [see Warnings and Precautions (5.1)]
• QT Prolongation [see Warnings and Precautions (5.2)]
• Serotonin Syndrome [see Warnings and Precautions (5.3)]

• Myocardial Ischemia [see Warnings and Precautions (5.4)]

• Masking of Progressive Ileus and Gastric Distension [see Warnings and Precautions (5.5)]

6.1 Clinical Trials Experience

Because clinical trials are conducted under widely varying conditions, adverse reaction rates observed in the clinical trials of a drug cannot be directly compared with rates in the clinical trials of another drug and may not reflect the rates observed in clinical practice.

The following adverse reactions have been reported in clinical trials of adult patients treated with ondansetron, the active ingredient of intravenous ondansetron injection across a range of dosages. A causal relationship to therapy with ondansetron injection was unclear in many cases.

Chemotherapy-Induced Nausea and Vomiting

Table 2: Adverse Reactions Reported in >5% of Adult Patients Who Received Ondansetron at a Dosage of Three 0.15-mg/kg Doses

Adverse Reaction | Number of Adult Patients With Reaction
Adverse Reaction | Ondansetron Injection 0.15 mg/kg x 3 (n = 419) | Metoclopramide (n = 156) | Placebo (n = 34)
Diarrhea | 16% | 44% | 18%
Headache | 17% | 7% | 15%
Fever | 8% | 5% | 3%

Cardiovascular: Rare cases of angina (chest pain), electrocardiographic alterations, hypotension, and tachycardia have been reported.

Gastrointestinal: Constipation has been reported in 11% of chemotherapy patients receiving multiday ondansetron.

Hepatic: In comparative trials in cisplatin chemotherapy patients with normal baseline values of aspartate transaminase (AST) and alanine transaminase (ALT), these enzymes have been reported to exceed twice the upper limit of normal in approximately 5% of patients. The increases were transient and did not appear to be related to dose or duration of therapy. On repeat exposure, similar transient elevations in transaminase values occurred in some courses, but symptomatic hepatic disease did not occur.

Integumentary: Rash has occurred in approximately 1% of patients receiving ondansetron.

Neurological: There have been rare reports consistent with, but not diagnostic of, extrapyramidal reactions in patients receiving ondansetron injection, and rare cases of grand mal seizure.

Other: Rare cases of hypokalemia have been reported.

Postoperative Nausea and/or Vomiting
The adverse reactions in Table 3 have been reported in ≥2% of adults receiving ondansetron at a dosage of 4 mg intravenous over 2 to 5 minutes in clinical trials.

Table 3: Adverse Reactions Reported in ≥ 2% (and with greater frequency than the placebo group) of Adult Patients Receiving Ondansetron at a Dosage of 4 mg Intravenous Over 2 to 5 Minutes

Adverse Reaction^1,2 | Ondansetron Injection 4 mg Intravenous (n = 547) | Placebo (n = 547)
Headache | 92 (17%) | 77 (14%)
Drowsiness/Sedation | 44 (8%) | 37 (7%)
Injection-site reaction | 21 (4%) | 18 (3%)
Fever | 10 (2%) | 6 (1%)
Cold sensation | 9 (2%) | 8 (1%)
Pruritus | 9 (2%) | 3 (< 1%)
Paresthesia | 9 (2%) | 2 (< 1%)

^1. Adverse reactions: Rates of these reactions were not significantly different in the ondansetron and placebo groups.

^2. Patients were receiving multiple concomitant perioperative and postoperative medications.

Pediatric Use: Rates of adverse reactions were similar in both the ondansetron and placebo groups in pediatric patients receiving ondansetron (a single 0.1-mg/kg dose for pediatric patients weighing 40 kg or less, or 4 mg for pediatric patients weighing more than 40 kg) administered intravenously over at least 30 seconds. Diarrhea was seen more frequently in patients taking ondansetron injection (2%) compared with placebo (<1%) in the 1-month to 24-month age-group. These patients were receiving multiple concomitant perioperative and postoperative medications.

6.2 Postmarketing Experience

The following adverse reactions have been identified during postapproval use of ondansetron. Because these reactions are reported voluntarily from a population of uncertain size, it is not always possible to reliably estimate their frequency or establish a causal relationship to drug exposure. The reactions have been chosen for inclusion due to a combination of their seriousness, frequency of reporting, or potential causal connection to ondansetron.

Cardiovascular
Arrhythmias (including ventricular and supraventricular tachycardia, premature ventricular contractions, and atrial fibrillation), bradycardia, electrocardiographic alterations (including second-degree heart block, QT/QTc interval prolongation, and ST segment depression), palpitations, and syncope. Rarely and predominantly with intravenous ondansetron, transient ECG changes, including QT/QTc interval prolongation have been reported [see Warnings and Precautions (5.2)].

Myocardial ischemia was reported predominately with intravenous administration [see Warnings and Precautions (5.4)].

General
Flushing: Rare cases of hypersensitivity reactions, sometimes severe (e.g., anaphylactic reactions, angioedema, bronchospasm, cardiopulmonary arrest, hypotension, laryngeal edema, laryngospasm, shock, shortness of breath, stridor) have also been reported. A positive lymphocyte transformation test to ondansetron has been reported, which suggests immunologic sensitivity to ondansetron.

Hepatobiliary
Liver enzyme abnormalities have been reported. Liver failure and death have been reported in patients with cancer receiving concurrent medications, including potentially hepatotoxic cytotoxic chemotherapy and antibiotics.

Local Reactions
Pain, redness, and burning at site of injection.

Lower Respiratory
Hiccups.

Neurological
Oculogyric crisis, appearing alone, as well as with other dystonic reactions. Transient dizziness during or shortly after intravenous infusion.

Skin
Urticaria, Stevens-Johnson syndrome, and toxic epidermal necrolysis.

Eye Disorders
Cases of transient blindness, predominantly during intravenous administration, have been reported. These cases of transient blindness were reported to resolve within a few minutes up to 48 hours. Transient blurred vision, in some cases associated with abnormalities of accommodation, has also been reported.

7 DRUG INTERACTIONS

7.1 Drugs Affecting Cytochrome P-450 Enzymes

Ondansetron does not appear to induce or inhibit the cytochrome P-450 drug-metabolizing enzyme system of the liver. Because ondansetron is metabolized by hepatic cytochrome P-450 drug-metabolizing enzymes (CYP3A4, CYP2D6, CYP1A2), inducers or inhibitors of these enzymes may change the clearance and, hence, the half-life of ondansetron [see Clinical Pharmacology (12.3)]. On the basis of limited available data, no dosage adjustment is recommended for patients on these drugs.

7.2 Apomorphine

Based on reports of profound hypotension and loss of consciousness when apomorphine was administered with ondansetron, the concomitant use of apomorphine with ondansetron is contraindicated [see Contraindications (4)].

7.3 Phenytoin, Carbamazepine, and Rifampin

In patients treated with potent inducers of CYP3A4 (i.e., phenytoin, carbamazepine, and rifampin), the clearance of ondansetron was significantly increased and ondansetron blood concentrations were decreased. However, on the basis of available data, no dosage adjustment for ondansetron is recommended for patients on these drugs [see Clinical Pharmacology (12.3)].

7.4 Tramadol

Although there are no data on pharmacokinetic drug interactions between ondansetron and tramadol, data from two small trials indicate that concomitant use of ondansetron may result in reduced analgesic activity of tramadol. Patients on concomitant ondansetron self-administered tramadol more frequently in these trials, leading to an increased cumulative dose in patient-controlled administration of tramadol.

7.5 Serotonergic Drugs

Serotonin syndrome (including altered mental status, autonomic instability, and neuromuscular symptoms) has been described following the concomitant use of 5-HT3 receptor antagonists and other serotonergic drugs, including SSRIs and SNRIs [see Warnings and Precautions (5.3)].

7.6 Chemotherapy

In humans, carmustine, etoposide, and cisplatin do not affect the pharmacokinetics of ondansetron.

In a crossover trial in 76 pediatric patients, intravenous ondansetron did not increase blood levels of high-dose methotrexate.

7.7 Temazepam

The coadministration of ondansetron had no effect on the pharmacokinetics and pharmacodynamics of temazepam.

7.8 Alfentanil and Atracurium

Ondansetron does not alter the respiratory depressant effects produced by alfentanil or the degree of neuromuscular blockade produced by atracurium. Interactions with general or local anesthetics have not been studied.

8 USE IN SPECIFIC POPULATIONS

8.1 Pregnancy

Risk Summary
Published epidemiological studies on the association between ondansetron use and major birth defects have reported inconsistent findings and have important methodological limitations that preclude conclusions about the safety of ondansetron use in pregnancy (see Data). Available postmarketing data have not identified a drug-associated risk of miscarriage or adverse maternal outcomes. Reproductive studies in rats and rabbits did not show evidence of harm to the fetus when ondansetron was administered intravenously during organogenesis at approximately 3.6 and 2.9 times the maximum recommended human intravenous dose of 0.15 mg/kg given three times a day, based on body surface area (BSA), respectively (see Data).
The background risk of major birth defects and miscarriage for the indicated population is unknown. All pregnancies have a background risk of birth defect, miscarriages, or other adverse outcomes. In the US general population, the estimated background risk of major birth defects and miscarriages in clinically recognized pregnancies is 2% to 4% and 15% to 20%, respectively.

Data
Human Data

Available data on ondansetron use in pregnant women from several published epidemiological studies preclude an assessment of a drug-associated risk of adverse fetal outcomes due to important methodological limitations, including the uncertainty of whether women who filled a prescription actually took the medication, the concomitant use of other medications or treatments, recall bias, and other unadjusted confounders.
Ondansetron exposure in utero has not been associated with overall major congenital malformations in aggregate analyses. One large retrospective cohort study examined 1970 women who received a prescription for ondansetron during pregnancy and reported no association between ondansetron exposure and major congenital malformations, miscarriage, stillbirth, preterm delivery, infants of low birth weight, or infants small for gestational age.

Two large retrospective cohort studies and one case-control study have assessed ondansetron exposure in the first trimester and risk of cardiovascular defects with inconsistent findings. Relative risks (RR) ranged from 0.97 (95% CI 0.86 to 1.10) to 1.62 (95% CI 1.04, 2.54). A subset analysis in one of the cohort studies observed that ondansetron was specifically associated with cardiac septal defects (RR 2.05, 95% CI 1.19, 3.28); however this association was not confirmed in other studies.

Several studies have assessed ondansetron and the risk of oral clefts with inconsistent findings. A retrospective cohort study of 1.8 million pregnancies in the US Medicaid Database showed an increased risk of oral clefts among 88,467 pregnancies in which oral ondansetron was prescribed in the first trimester (RR 1.24, 95% CI 1.03, 1.48), but no such association was reported with intravenous ondansetron in 23,866 pregnancies (RR 0.95, 95% CI 0.63, 1.43). In the subgroup of women who received both forms of administration, the RR was 1.07 (95% CI 0.59, 1.93). Two case-control studies, using data from birth defects surveillance programs, reported conflicting associations between maternal use of ondansetron and isolated cleft palate (OR 1.6 [95% CI 1.1, 2.3] and 0.5 [95% CI 0.3, 1.0]). It is unknown whether ondansetron exposure in utero in the cases of cleft palate occurred during the time of palate formation (the palate is formed between the 6th and 9th weeks of pregnancy).

Animal Data

In embryo-fetal development studies in rats and rabbits, pregnant animals received intravenous doses of ondansetron up to 10 mg/kg/day and 4 mg/kg/day, respectively, during the period of organogenesis. With the exception of short periods of maternal weight loss and a slight increase in the incidence of early uterine deaths at the high dose level in rabbits, there were no significant effects of ondansetron on the maternal animals or the development of the offspring. At doses of 10 mg/kg/day in rats and 4 mg/kg/day in rabbits, the maternal exposure margin was approximately 3.6 and 2.9 times the maximum recommended human oral dose of 0.15 mg/kg given three times a day, respectively, based on BSA.
No intravenous pre- and post-natal developmental toxicity study was performed with ondansetron. In an oral pre- and post-natal development study pregnant rats received oral doses of ondansetron up to 15 mg/kg/day from Day 17 of pregnancy to litter Day 21. With the exception of a slight reduction in maternal body weight gain, there were no effects upon the pregnant rats and the pre- and postnatal development of their offspring, including reproductive performance of the mated F1 generation.

8.2 Lactation

Risk Summary

Ondansetron is unlikely to result in clinically relevant exposures in breastfed infants when administered intravenously at doses up to 4 mg/day to women who are breastfeeding. Available data from a lactation study involving pharmacokinetic samples from 80 lactating women and 20 infants
indicate that ondansetron is present at low levels in human milk and in the plasma of breastfed infants. Both the estimated daily infant dose (DID) of ondansetron (0.002 mg/kg/day), and the relative infant dose (RID) (3.7%) were low (see Data).

In the same study, no adverse effects attributed to ondansetron were reported in infants exposed to ondansetron through breast milk. There are no data on the effects of ondansetron on milk production.

Data

A pharmacokinetic study utilizing opportunistic sampling of a convenience sample of 80 lactating women receiving intravenous ondansetron for the treatment of post-operative nausea and vomiting and 20 breastfed infants showed that ondansetron was present in breast milk with an ave rage milk to plasma ratio of 0.91 following a median (range) dose of ondansetron of 4 (4 to 8) mg/dose. Usingthe average milk concentration over 24 hours to estimate the DID and the RID, the DID was 0.002 mg/kg/day and the RID was 3.7% of a weight-adjusted single maternal dose of 4 mg. Among the 20 infant plasma samples, seven concentrations (35%) were below the limit of quantification. Among the 13 infants with a quantifiable plasma concentration, the median (range) concentration was 0.78 (0 to 7.2) ng/mL. The highest observed concentration among these 13 infants was approximately 10 times lower than the median maximum concentration (76.6 ng/mL) observed in an open-label, single-dose pharmacokinetic study conducted in pediatric surgical patients aged 1 to 24 months who received a single 0.1 mg/kg dose of intravenous ondansetron.

8.4 Pediatric Use

Little information is available about the use of ondansetron in pediatric surgical patients younger than 1 month [see Clinical Studies (14.2)]. Little information is available about the use of ondansetron in pediatric cancer patients younger than 6 months [see Clinical Studies (14.1), Dosage and Administration (2)].

The clearance of ondansetron in pediatric patients aged 1 month to 4 months is slower and the half-life is ~2.5-fold longer than patients who are aged >4 to 24 months. As a precaution, it is recommended that patients younger than 4 months receiving this drug be closely monitored [see Clinical Pharmacology (12.3)].

8.5 Geriatric Use

Of the total number of subjects enrolled in cancer chemotherapy-induced and postoperative nausea and vomiting US- and foreign-controlled clinical trials, 862 were aged 65 years and older. No overall differences in safety or effectiveness were observed between subjects 65 years and older and younger subjects. A reduction in clearance and increase in elimination half-life were seen in patients older than 75 years compared with younger subjects [see Clinical Pharmacology (12.3)]. There were an insufficient number of patients older than 75 years of age and older in the clinical trials to permit safety or efficacy conclusions in this age-group. Other reported clinical experience has not identified differences in responses between the elderly and younger patients, but greater sensitivity of some older individuals cannot be ruled out. Dosage adjustment is not needed in patients over the age of 65.

8.6 Hepatic Impairment

In patients with severe hepatic impairment (Child-Pugh score of 10 or greater), clearance is reduced and apparent volume of distribution is increased with a resultant increase in plasma half-life [see Clinical Pharmacology (12.3)]. In such patients, a total daily dose of 8 mg should not be exceeded [see Dosage and Administration (2.3)].

8.7 Renal Impairment

Although plasma clearance is reduced in patients with severe renal impairment (creatinine clearance <30 mL/min), no dosage adjustment is recommended [see Clinical Pharmacology (12.3)].

9 DRUG ABUSE AND DEPENDENCE

Animal studies have shown that ondansetron is not discriminated as a benzodiazepine nor does it substitute for benzodiazepines in direct addiction studies.

10 OVERDOSAGE

There is no specific antidote for ondansetron overdose. Patients should be managed with appropriate supportive therapy. Individual intravenous doses as large as 150 mg and total daily intravenous doses as large as 252 mg have been inadvertently administered without significant adverse events. These doses are more than 10 times the recommended daily dose.

In addition to the adverse reactions listed above, the following events have been described in the setting of ondansetron overdose: “Sudden blindness” (amaurosis) of 2 to 3 minutes’ duration plus severe constipation occurred in one patient that was administered 72 mg of ondansetron intravenously as a single dose. Hypotension (and faintness) occurred in another patient that took 48 mg of ondansetron hydrochloride tablets. Following infusion of 32 mg over only a 4-minute period, a vasovagal episode with transient second-degree heart block was observed. In all instances, the events resolved completely.

Pediatric cases consistent with serotonin syndrome have been reported after inadvertent oral overdoses of ondansetron (exceeding estimated ingestion of 5 mg/kg) in young children. Reported symptoms included somnolence, agitation, tachycardia, tachypnea, hypertension, flushing, mydriasis, diaphoresis, myoclonic movements, horizontal nystagmus, hyperreflexia, and seizure. Patients required supportive care, including intubation in some cases, with complete recovery without sequelae within 1 to 2 days.

11 DESCRIPTION

The active ingredient of Ondansetron Injection, USP is ondansetron hydrochloride, a selective blocking agent of the serotonin 5-HT3 receptor type. Its chemical name is (±) 1, 2, 3, 9-tetrahydro-9-methyl-3-[(2-methyl-1H-imidazol-1-yl)methyl]-4H-carbazol-4-one, monohydrochloride, dihydrate. It has the following structural formula:

The empirical formula is C18H19N3O•HCl•2H2O, representing a molecular weight of 365.9 g/mol.

Ondansetron HCl is a white to off-white powder that is soluble in water and normal saline.

Each 1 mL of aqueous solution in the 2 mL single-dose vial contains 2 mg of ondansetron as the hydrochloride dihydrate; 9 mg of sodium chloride, USP; and 0.5 mg of citric acid monohydrate, USP and 0.25 mg of sodium citrate dihydrate, USP as buffers in Water for Injection, USP.

Each 1 mL of aqueous solution in the 20 mL multi-dose vial contains 2 mg of ondansetron as the hydrochloride dihydrate; 8.3 mg of sodium chloride, USP; 0.5 mg of citric acid monohydrate, USP and 0.25 mg of sodium citrate dihydrate, USP as buffers; and 1.2 mg of methylparaben, NF and 0.15 mg of propylparaben, NF as preservatives in Water for Injection, USP.

Ondansetron Injection, USP is a clear, colorless, nonpyrogenic, sterile solution for intravenous or intramuscular use. The pH of the injection solution is 3.3 to 4.0.

12 CLINICAL PHARMACOLOGY

12.1 Mechanism of Action

Ondansetron is a selective 5-HT3 receptor antagonist. While ondansetron’s mechanism of action has not been fully characterized, it is not a dopamine-receptor antagonist.

12.2 Pharmacodynamics

In normal volunteers, single intravenous doses of 0.15 mg/kg of ondansetron had no effect on esophageal motility, gastric motility, lower esophageal sphincter pressure, or small intestinal transit time. In another trial in 6 normal male volunteers, a 16 mg dose infused over 5 minutes showed no effect of the drug on cardiac output, heart rate, stroke volume, blood pressure, or ECG. Multiday administration of ondansetron has been shown to slow colonic transit in normal volunteers. Ondansetron has no effect on plasma prolactin concentrations. In a gender balanced pharmacodynamic trial (n = 56), ondansetron 4 mg administered intravenously or intramuscularly was dynamically similar in the prevention of nausea and vomiting using the ipecacuanha model of emesis.

Cardiac Electrophysiology
QTc interval prolongation was studied in a double-blind, single intravenous dose, placebo- and positive-controlled, crossover trial in 58 healthy subjects. The maximum mean (95% upper confidence bound) difference in QTcF from placebo after baseline correction was 19.5 (21.8) ms and 5.6 (7.4) ms after 15-minute intravenous infusions of 32 mg and 8 mg ondansetron, respectively. A significant exposure-response relationship was identified between ondansetron concentration and ΔΔQTcF. Using the established exposure-response relationship, 24 mg infused intravenously over 15 minutes had a mean predicted (95% upper prediction interval) ΔΔQTcF of 14.0 (16.3) ms. In contrast, 16 mg infused intravenously over 15 minutes using the same model had a mean predicted (95% upper prediction interval) ΔΔQTcF of 9.1 (11.2) ms. In this study, the 8-mg dose infused over 15 minutes did not prolong the QT interval to any clinically relevant extent.

12.3 Pharmacokinetics

In normal adult volunteers, the following mean pharmacokinetic data have been determined following a single 0.15-mg/kg intravenous dose.

Table 4: Pharmacokinetics in Normal Adult Volunteers

Age-group (years) | n | Peak Plasma Concentration (ng/mL) | Mean Elimination Half-life (h) | Plasma Clearance (L/h/kg)
19 to 40 | 11 | 102 | 3.5 | 0.381
61 to 74 | 12 | 106 | 4.7 | 0.319
≥75 | 11 | 170 | 5.5 | 0.262

Absorption

A trial was performed in normal volunteers (n = 56) to evaluate the pharmacokinetics of a single 4-mg dose administered as a 5-minute infusion compared with a single intramuscular injection. Systemic exposure as measured by mean area under curve (AUC) were equivalent, with values of 156 [95% CI 136, 180] and 161 [95% CI 137, 190] ng•h/mL for intravenous and intramuscular groups, respectively. Mean peak plasma concentrations were 42.9 [95% CI 33.8, 54.4] ng/mL at 10 minutes after intravenous infusion and 31.9 [95% CI 26.3, 38.6] ng/mL at 41 minutes after intramuscular injection.

Distribution

Plasma protein binding of ondansetron as measured in vitro was 70% to 76%, over the pharmacologic concentration range of 10 to 500 ng/mL. Circulating drug also distributes into erythrocytes.

Elimination

Metabolism: Ondansetron is extensively metabolized in humans, with approximately 5% of a radiolabeled dose recovered as the parent compound from the urine. The primary metabolic pathway is hydroxylation on the indole ring followed by subsequent glucuronide or sulfate conjugation.

Although some nonconjugated metabolites have pharmacologic activity, these are not found in plasma at concentrations likely to significantly contribute to the biological activity of ondansetron. The metabolites are observed in the urine.

In vitro metabolism studies have shown that ondansetron is a substrate for multiple human hepatic cytochrome P-450 enzymes, including CYP1A2, CYP2D6, and CYP3A4. In terms of overall ondansetron turnover, CYP3A4 plays a predominant role while formation of the major in vivo metabolites is apparently mediated by CYP1A2. The role of CYP2D6 in ondansetron in vivo metabolism is relatively minor.

The pharmacokinetics of intravenous ondansetron did not differ between subjects who were poor metabolizers of CYP2D6 and those who were extensive metabolizers of CYP2D6, further supporting the limited role of CYP2D6 in ondansetron disposition in vivo.

Excretion: In adult cancer patients, the mean ondansetron elimination half-life was 4.0 hours, and there was no difference in the multidose pharmacokinetics over a 4-day period. In a dose-proportionality trial, systemic exposure to 32 mg of ondansetron was not proportional to dose as measured by comparing dose-normalized AUC values with an 8-mg dose. This is consistent with a small decrease in systemic clearance with increasing plasma concentrations.

Specific Populations

Geriatric Patients: A reduction in clearance and increase in elimination half-life are seen in patients older than 75 years of age [see Use in Specific Populations (8.5)].

Pediatric Patients: Pharmacokinetic samples were collected from 74 cancer patients aged 6 to 48 months, who received a dose of 0.15 mg/kg of intravenous ondansetron every 4 hours for 3 doses during a safety and efficacy trial. These data were combined with sequential pharmacokinetics data from 41 surgery patients aged 1 month to 24 months, who received a single dose of 0.1 mg/kg of intravenous ondansetron prior to surgery with general anesthesia, and a population pharmacokinetic analysis was performed on the combined data set. The results of this analysis are included in Table 5 and are compared with the pharmacokinetic results in cancer patients aged 4 to 18 years.

Table 5: Pharmacokinetics in Pediatric Cancer Patients Aged 1 Month to 18 Years

Subjects and Age-group | N | CL (L/h/kg) | Vdss (L/kg) | t½ (h)
Subjects and Age-group | N | Geometric Mean |  | Mean
Pediatric Cancer Patients 4 to 18 years | N = 21 | 0.599 | 1.9 | 2.8
Population PK Patients^1 1 month to 48 months | N = 115 | 0.582 | 3.65 | 4.9

^1 Population PK (Pharmacokinetic) Patients: 64% cancer patients and 36% surgery patients.

Based on the population pharmacokinetic analysis, cancer patients aged 6 to 48 months who receive a dose of 0.15 mg/kg of intravenous ondansetron every 4 hours for 3 doses would be expected to achieve a systemic exposure (AUC) consistent with the exposure achieved in previous pediatric trials in cancer patients (4 to 18 years) at similar doses.

In a trial of 21 pediatric patients (3 to 12 years) who were undergoing surgery requiring anesthesia for a duration of 45 minutes to 2 hours, a single intravenous dose of ondansetron, 2 mg (3 to 7 years) or 4 mg (8 to 12 years), was administered immediately prior to anesthesia induction. Mean weight-normalized clearance and volume of distribution values in these pediatric surgical patients were similar to those previously reported for young adults. Mean terminal half-life was slightly reduced in pediatric patients (range, 2.5 to 3 hours) in comparison with adults (range, 3 to 3.5 hours).

In a trial of 51 pediatric patients (aged 1 month to 24 months) who were undergoing surgery requiring general anesthesia, a single intravenous dose of ondansetron, 0.1 or 0.2 mg/kg, was administered prior to surgery. As shown in Table 6, the 41 patients with pharmacokinetic data were divided into 2 groups, patients aged 1 month to 4 months and patients aged 5 to 24 months, and are compared with pediatric patients aged 3 to 12 years.

Table 6: Pharmacokinetics in Pediatric Surgery Patients Aged 1 Month to 12 Years

Subjects and Age-group | N | CL (L/h/kg) | Vdss (L/kg) | t½ (h)
Subjects and Age-group | N | Geometric Mean |  | Mean
Pediatric Surgery Patients 3 to 12 years | N = 21 | 0.439 | 1.65 | 2.9
Pediatric Surgery Patients 5 to 24 months | N = 22 | 0.581 | 2.3 | 2.9
Pediatric Surgery Patients 1 month to 4 months | N = 19 | 0.401 | 3.5 | 6.7

In general, surgical and cancer pediatric patients younger than 18 years tend to have a higher ondansetron clearance compared with adults leading to a shorter half-life in most pediatric patients. In patients aged 1 month to 4 months, a longer half-life was observed due to the higher volume of distribution in this age-group.

In a trial of 21 pediatric cancer patients (aged 4 to 18 years) who received three intravenous doses of 0.15 mg/kg of ondansetron at 4-hour intervals, patients older than 15 years exhibited ondansetron pharmacokinetic parameters similar to those of adults.

Patients with Renal Impairment: Due to the very small contribution (5%) of renal clearance to the overall clearance, renal impairment was not expected to significantly influence the total clearance of ondansetron. However, ondansetron mean plasma clearance was reduced by about 41% in patients with severe renal impairment (creatinine clearance <30 mL/min). This reduction in clearance is variable and was not consistent with an increase in half-life [see Use in Specific Populations (8.7)].

Patients with Hepatic Impairment: In patients with mild-to-moderate hepatic impairment, clearance is reduced 2-fold and mean half-life is increased to 11.6 hours compared with 5.7 hours in those without hepatic impairment. In patients with severe hepatic impairment (Child-Pugh score of 10 or greater), clearance is reduced 2-fold to 3-fold and apparent volume of distribution is increased with a resultant increase in half-life to 20 hours [see Dosage and Administration (2.3), Use in Specific Populations (8.6)].

Drug Interaction Studies
CYP3A4 Inducers: Ondansetron elimination may be affected by cytochrome P-450 inducers. In a pharmacokinetic trial of 16 epileptic patients maintained chronically on CYP3A4 inducers, carbamazepine, or phenytoin, a reduction in AUC, Cmax, and t½ of ondansetron was observed. This resulted in a significant increase in the clearance of ondansetron. In a pharmacokinetic study of 10 healthy subjects receiving a single-dose intravenous dose of ondansetron 8 mg after 600 mg rifampin once daily for five days, the AUC and the t½ of ondansetron were reduced by 48% and 46%, respectively. These changes in ondansetron exposure with CYP3A4 inducers are not thought to be clinically relevant [see Drug Interactions (7.3)].

Chemotherapeutic Agents: Carmustine, etoposide, and cisplatin do not affect the pharmacokinetics of ondansetron [see Drug Interactions (7.6)].

13 NONCLINICAL TOXICOLOGY

13.1 Carcinogenesis, Mutagenesis, Impairment of Fertility

Carcinogenic effects were not seen in 2-year studies in rats and mice with oral ondansetron doses up to 10 and 30 mg/kg per day, respectively (approximately 3.6 and 5.4 times the recommended human intravenous dose of 0.15 mg/kg given three times a day, based on BSA). Ondansetron was not mutagenic in standard tests for mutagenicity.

Oral administration of ondansetron up to 15 mg/kg per day (approximately 3.8 times the recommended human intravenous dose, based on BSA) did not affect fertility or general reproductive performance of male and female rats.

14 CLINICAL STUDIES

The clinical efficacy of ondansetron hydrochloride, the active ingredient of ondansetron injection, was assessed in clinical trials as described below.

14.1 Chemotherapy-Induced Nausea and Vomiting

Adults

In a double-blind trial of three different dosing regimens of ondansetron injection, 0.015 mg/kg, 0.15 mg/kg, and 0.30 mg/kg, each given three times during the course of cancer chemotherapy, the 0.15-mg/kg dosing regimen was more effective than the 0.015-mg/kg dosing regimen. The 0.30-mg/kg dosing regimen was not shown to be more effective than the 0.15-mg/kg dosing regimen.

Cisplatin-Based Chemotherapy: In a double-blind trial in 28 patients, ondansetron injection (three 0.15-mg/kg doses) was significantly more effective than placebo in preventing nausea and vomiting induced by cisplatin-based chemotherapy. Therapeutic response was as shown in Table 7.

Table 7: Therapeutic Response in Prevention of Chemotherapy-Induced Nausea and Vomiting in Single-day Cisplatin Therapy^1 in Adults

 | Ondansetron Injection (0.15 mg/kg x 3) | Placebo | P-value^2
Number of patients | 14 | 14
Treatment response 0 Emetic episodes 1 to 2 Emetic episodes 3 to 5 Emetic episodes More than 5 emetic episodes/rescued | 2 (14%) 8 (57%) 2 (14%) 2 (14%) | 0 (0%) 0 (0%) 1 (7%) 13 (93%) | 0.001
Median number of emetic episodes | 1.5 | Undefined^3
Median time to first emetic episode (h) | 11.6 | 2.8 | 0.001
Median nausea scores (0 to 100)^4 | 3 | 59 | 0.034
Global satisfaction with control of nausea and vomiting (0 to 100)^5 | 96 | 10.5 | 0.009

^1. Chemotherapy was high dose (100 and 120 mg/m^2; ondansetron injection n = 6, placebo n = 5) or moderate dose (50 and 80 mg/m^2; ondansetron injection n = 8, placebo n = 9). Other chemotherapeutic agents included fluorouracil, doxorubicin, and cyclophosphamide. There was no difference between treatments in the types of chemotherapy that would account for differences in response.
^2. Efficacy based on "all-patients-treated" analysis.
^3. Median undefined since at least 50% of the patients were rescued or had more than five emetic episodes.
4.Visual analog scale assessment of nausea: 0 = no nausea, 100 = nausea as bad as it can be.
^5. Visual analog scale assessment of satisfaction: 0 = not at all satisfied, 100 = totally satisfied.

Ondansetron injection (0.15-mg/kg x 3 doses) was compared with metoclopramide (2 mg/kg x 6 doses) in a single-blind trial in 307 patients receiving cisplatin ≥100 mg/m^2 with or without other chemotherapeutic agents. Patients received the first dose of ondansetron or metoclopramide 30 minutes before cisplatin. Two additional ondansetron doses were administered 4 and 8 hours later, or five additional metoclopramide doses were administered 2, 4, 7, 10, and 13 hours later. Cisplatin was administered over a period of 3 hours or less. Episodes of vomiting and retching were tabulated over the period of 24 hours after cisplatin. The results of this trial are summarized in Table 8.

Table 8: Therapeutic Response in Prevention of Vomiting Induced by Cisplatin (≥100 mg/m^2) Single-day Therapy^1 in Adults

 | Ondansetron Injection 0.15 mg/kg x 3 | Metoclopramide 2 mg/kg x 6 | P -value
Number of patients in efficacy population | 136 | 138
Treatment response 0 Emetic episodes 1 to 2 Emetic episodes 3 to 5 Emetic episodes More than 5 emetic episodes/rescued | 54 (40%) 34 (25%) 19 (14%) 29 (21%) | 41 (30%) 30 (22%) 18 (13%) 49 (36%)
Comparison of treatments with respect to 0 Emetic episodes More than 5 emetic episodes/rescued | 54/136 29/136 | 41/138 49/138 | 0.083 0.009
Median number of emetic episodes | 1 | 2 | 0.005
Median time to first emetic episode (h) | 20.5 | 4.3 | < 0.001
Global satisfaction with control of nausea and vomiting (0 to 100)^2 | 85 | 63 | 0.001
Acute dystonic reactions | 0 | 8 | 0.005
Akathisia | 0 | 10 | 0.002

^1. In addition to cisplatin, 68% of patients received other chemotherapeutic agents, including cyclophosphamide, etoposide, and fluorouracil. There was no difference between treatments in the types of chemotherapy that would account for differences in response.
^2. Visual analog scale assessment: 0 = not at all satisfied, 100 = totally satisfied.

Cyclophosphamide-Based Chemotherapy: In a double-blind, placebo-controlled trial of ondansetron injection (three 0.15-mg/kg doses) in 20 patients receiving cyclophosphamide (500 to 600 mg/m2) chemotherapy, ondansetron injection was significantly more effective than placebo in preventing nausea and vomiting. The results are summarized in Table 9.
Table 9: Therapeutic Response in Prevention of Chemotherapy-Induced Nausea and Vomiting in Single-day Cyclophosphamide Therapy^1 in Adults

 | Ondansetron Injection (0.15 mg/kg x 3) | Placebo | P-value^2
Number of patients | 10 | 10
Treatment response 0 Emetic episodes 1 to 2 Emetic episodes 3 to 5 Emetic episodes More than 5 emetic episodes/rescued | 7 (70%) 0 (0%) 2 (20%) 1 (10%) | 0 (0%) 2 (20%) 4 (40%) 4 (40%) | 0.001 0.131
Median number of emetic episodes | 0 | 4 | 0.008
Median time to first emetic episode (h) | Undefined^3 | 8.79
Median nausea scores (0 to 100)^4 | 0 | 60 | 0.001
Global satisfaction with control of nausea and vomiting (0 to 100)^5 | 100 | 52 | 0.008

^1 Chemotherapy consisted of cyclophosphamide in all patients, plus other agents, including fluorouracil, doxorubicin, methotrexate, and vincristine. There was no difference between treatments in the type of chemotherapy that would account for differences in response.
^2 Efficacy based on "all-patients-treated" analysis.
^3 Median undefined since at least 50% of patients did not have any emetic episodes.
^4Visual analog scale assessment of nausea: 0 = no nausea, 100 = nausea as bad as it can be.
^5 Visual analog scale assessment of satisfaction: 0 = not at all satisfied, 100 = totally satisfied.

Re-treatment: In uncontrolled trials, 127 patients receiving cisplatin (median dose, 100 mg/m^2) and ondansetron who had two or fewer emetic episodes were re-treated with ondansetron and chemotherapy, mainly cisplatin, for a total of 269 re-treatment courses (median: 2; range, 1 to 10). No emetic episodes occurred in 160 (59%), and two or fewer emetic episodes occurred in 217 (81%) re-treatment courses.

Pediatrics
Four open-label, noncomparative (one US, three foreign) trials have been performed with 209 pediatric cancer patients aged 4 to 18 years given a variety of cisplatin or noncisplatin regimens. In the three foreign trials, the initial dose of ondansetron injection ranged from 0.04 to 0.87 mg/kg for a total dose of 2.16 to 12 mg. This was followed by the oral administration of ondansetron ranging from 4 to 24 mg daily for 3 days. In the US trial, ondansetron injection was administered intravenously (only) in three doses of 0.15 mg/kg each for a total daily dose of 7.2 to 39 mg. In these trials, 58% of the 196 evaluable patients had a complete response (no emetic episodes) on Day 1. Thus, prevention of vomiting in these pediatric patients was essentially the same as for patients older than 18 years.

An open-label, multicenter, noncomparative trial has been performed in 75 pediatric cancer patients aged 6 to 48 months receiving at least one moderately or highly emetogenic chemotherapeutic agent. Fifty-seven percent (57%) were females; 67% were white, 18% were American Hispanic, and 15% were black patients. Ondansetron injection was administered intravenously over 15 minutes in three doses of 0.15 mg/kg. The first dose was administered 30 minutes before the start of chemotherapy; the second and third doses were administered 4 and 8 hours after the first dose, respectively. Eighteen patients (25%) received routine prophylactic dexamethasone (i.e., not given as rescue). Of the 75 evaluable patients, 56% had a complete response (no emetic episodes) on Day 1. Thus, prevention of vomiting in these pediatric patients was comparable to the prevention of vomiting in patients aged 4 years and older.

14.2 Prevention of Postoperative Nausea and/or Vomiting

Adults
Adult surgical patients who received ondansetron immediately before the induction of general balanced anesthesia (barbiturate: thiopental, methohexital, or thiamylal; opioid: alfentanil or fentanyl; nitrous oxide; neuromuscular blockade: succinylcholine/curare and/or vecuronium or atracurium; and supplemental isoflurane) were evaluated in two double-blind US trials involving 554 patients. Ondansetron injection (4 mg) intravenous given over 2 to 5 minutes was significantly more effective than placebo. The results of these trials are summarized in Table 10.
Table 10: Therapeutic Response in Prevention of Postoperative Nausea and/or Vomiting in Adult Patients

 | Ondansetron 4 mg Intravenous | Placebo | P-value
Study 1
Emetic episodes: Number of patients Treatment response over 24-h postoperative period 0 Emetic episodes 1 Emetic episode More than 1 emetic episode/rescued | 136 103 (76%) 13 (10%) 20 (15%) | 139 64 (46%) 17 (12%) 58 (42%) | <0.001
Nausea assessments: Number of patients No nausea over 24-h postoperative period | 134 56 (42%) | 136 39 (29%)
Study 2
Emetic episodes: Number of patients Treatment response over 24-h postoperative period 0 Emetic episodes 1 Emetic episode More than 1 emetic episode/rescued | 136 85 (63%) 16 (12%) 35 (26%) | 143 63 (44%) 29 (20%) 51 (36%) | 0.002
Nausea assessments: Number of patients No nausea over 24-h postoperative period | 125 48 (38%) | 133 42 (32%)

The populations in Table 10 consisted mainly of females undergoing laparoscopic procedures.

In a placebo-controlled trial conducted in 468 males undergoing outpatient procedures, a single 4-mg intravenous ondansetron dose prevented postoperative vomiting over a 24-hour period in 79% of males receiving drug compared with 63% of males receiving placebo (P <0.001).

Two other placebo-controlled trials were conducted in 2,792 patients undergoing major abdominal or gynecological surgeries to evaluate a single 4-mg or 8-mg intravenous ondansetron dose for prevention of postoperative nausea and vomiting over a 24-hour period. At the 4-mg dosage, 59% of patients receiving ondansetron versus 45% receiving placebo in the first trial (P <0.001) and 41% of patients receiving ondansetron versus 30% receiving placebo in the second trial (P = 0.001) experienced no emetic episodes. No additional benefit was observed in patients who received intravenous ondansetron 8 mg compared with patients who received intravenous ondansetron 4 mg.

Pediatrics
Three double-blind, placebo-controlled trials have been performed (one US, two foreign) in 1,049 male and female patients (aged 2 to 12 years) undergoing general anesthesia with nitrous oxide. The surgical procedures included tonsillectomy with or without adenoidectomy, strabismus surgery, herniorrhaphy, and orchidopexy. Patients were randomized to either single intravenous doses of ondansetron (0.1 mg/kg for pediatric patients weighing 40 kg or less, 4 mg for pediatric patients weighing more than 40 kg) or placebo. Study drug was administered over at least 30 seconds, immediately prior to or following anesthesia induction. Ondansetron was significantly more effective than placebo in preventing nausea and vomiting. The results of these trials are summarized in Table 11.
Table 11: Therapeutic Response in Prevention of Postoperative Nausea and/or Vomiting in Pediatric Patients Aged 2 to 12 Years

Treatment Response Over 24 Hours | Ondansetron n (%) | Placebo n (%) | P-value
Study 1
Number of patients 0 Emetic episodes Failure^1 | 205 140 (68%) 65 (32%) | 210 82 (39%) 128 (61%) | ≤0.001
Study 2
Number of patients 0 Emetic episodes Failure^1 | 112 68 (61%) 44 (39%) | 110 38 (35%) 72 (65%) | ≤0.001
Study 3
Number of patients 0 Emetic episodes Failure^1 | 206 123 (60%) 83 (40%) | 206 96 (47%) 110 (53%) | ≤0.01
Nausea assessments^2 Number of patients None | 185 119 (64%) | 191 99 (52%) | ≤0.01

^1. Failure was one or more emetic episodes, rescued, or withdrawn.
^2. Nausea measured as none, mild, or severe.

A double-blind, multicenter, placebo-controlled trial was conducted in 670 pediatric patients aged 1 month to 24 months who were undergoing routine surgery under general anesthesia. Seventy-five percent (75%) were males; 64% were white, 15% were black, 13% were American Hispanic, 2% were Asian, and 6% were “other race” patients. A single 0.1-mg/kg intravenous dose of ondansetron administered within 5 minutes following induction of anesthesia was statistically significantly more effective than placebo in preventing vomiting. In the placebo group, 28% of patients experienced vomiting compared with 11% of subjects who received ondansetron (P ≤0.01). Overall, 32 (10%) of placebo patients and 18 (5%) of patients who received ondansetron received antiemetic rescue medication(s) or prematurely withdrew from the trial.

14.3 Prevention of Further Postoperative Nausea and/or Vomiting

Adults
Adult surgical patients receiving general balanced anesthesia (barbiturate: thiopental, methohexital, or thiamylal; opioid: alfentanil or fentanyl; nitrous oxide; neuromuscular blockade: succinylcholine/curare and/or vecuronium or atracurium; and supplemental isoflurane) who received no prophylactic antiemetics and who experienced nausea and/or vomiting within 2 hours postoperatively were evaluated in two double-blind US trials involving 441 patients. Patients who experienced an episode of postoperative nausea and/or vomiting were given ondansetron injection (4 mg) intravenously over 2 to 5 minutes, and this was significantly more effective than placebo. The results of these trials are summarized in Table 12.

Table 12: Therapeutic Response in Prevention of Further Postoperative Nausea and/or Vomiting in Adult Patients

 | Ondansetron 4 mg Intravenous | Placebo | P-value
Study 1
Emetic episodes: Number of patients Treatment response 24-h after study drug 0 Emetic episodes 1 Emetic episode More than 1 emetic episode/rescued Median time to first emetic episode (min)^1 | 104 49 (47%) 12 (12%) 43 (41%) 55.0 | 117 19 (16%) 9 (8%) 89 (76%) 43.0 | < 0.001
Nausea assessments: Number of patients Mean nausea score over 24 h postoperative period^2 | 98 1.7 | 102 3.1
Study 2
Emetic episodes: Number of patients Treatment response 24-h after study drug 0 Emetic episodes 1 Emetic episode More than 1 emetic episode/rescued Median time to first emetic episode (min)^1 | 112 49 (44%) 14 (13%) 49 (44%) 60.5 | 108 28 (26%) 3 (3%) 77 (71%) 34.0 | 0.006
Nausea assessments: Number of patients Mean nausea score over 24 h postoperative period^2 | 105 1.9 | 85 2.9

^1. After administration of study drug.
^2. Nausea measured on a scale of 0 to 10 with 0 = no nausea, 10 = nausea as bad as it can be.

The populations in Table 12 consisted mainly of women undergoing laparoscopic procedures.

Repeat Dosing in Adults: In patients who do not achieve adequate control of postoperative nausea and vomiting following a single, prophylactic, preinduction, intravenous dose of ondansetron 4 mg, administration of a second intravenous dose of ondansetron 4 mg postoperatively does not provide additional control of nausea and vomiting.

Pediatrics
One double-blind, placebo-controlled, US trial was performed in 351 male and female outpatients (aged 2 to 12 years) who received general anesthesia with nitrous oxide and no prophylactic antiemetics. Surgical procedures were unrestricted. Patients who experienced two or more emetic episodes within 2 hours following discontinuation of nitrous oxide were randomized to either single intravenous doses of ondansetron (0.1 mg/kg for pediatric patients weighing 40 kg or less, 4 mg for pediatric patients weighing more than 40 kg) or placebo administered over at least 30 seconds. Ondansetron was significantly more effective than placebo in preventing further episodes of nausea and vomiting. The results of the trial are summarized in Table 13.
Table 13: Therapeutic Response in Prevention of Further Postoperative Nausea and/or Vomiting in Pediatric Patients Aged 2 to 12 Years

Treatment Response Over 24 Hours | Ondansetron n (%) | Placebo n (%) | P-value
Number of patients 0 Emetic episodes Failure^1 | 180 96 (53%) 84 (47%) | 171 29 (17%) 142 (83%) | ≤ 0.001

1. Failure was one or more emetic episodes, rescued, or withdrawn.

16 HOW SUPPLIED/STORAGE AND HANDLING

Ondansetron Injection, USP, 2 mg per mL, is supplied as follows:

Ondansetron Injection, USP (Preservative-free)

NDC (2 mg per mL) Package Factor

23155-547-41 4 mg per 2 mL Single-Dose Vial 10 vials per carton
Ondansetron Injection, USP (Preservative-free)

NDC (2 mg per mL) Package Factor

23155-547-42 4 mg per 2 mL Single-Dose Vial 25 vials per carton
Ondansetron Injection, USP (Preservative)

NDC (2 mg per mL) Package Factor

23155-549-31 40 mg per 20 mL Multi-Dose Vial 1 vial per carton

Storage Conditions

Store at 20° to 25°C (68° to 77°F). [See USP Controlled Room Temperature.]

Protect from light. Retain in carton until time of use.
Sterile, Nonpyrogenic.
The container closure is not made with natural rubber latex.

17 PATIENT COUNSELING INFORMATION

Hypersensitivity Reactions

Inform patients that ondansetron injection may cause hypersensitivity reactions, some as severe as anaphylaxis and bronchospasm. The patient should report any signs and symptoms of hypersensitivity reactions, including fever, chills, rash, or breathing problems [see Warnings and Precautions (5.1)].

QT Prolongation

Patients should be informed that ondansetron injection may cause serious cardiac arrhythmias, such as QT prolongation. Patients should be instructed to tell their healthcare provider right away if they perceive a change in their heart rate, if they feel lightheaded, or if they have a syncopal episode.

Patients should be informed that the chances of developing severe cardiac arrhythmias, such as QT prolongation and Torsade de Pointes are higher in the following people:
• Patients with a personal or family history of abnormal heart rhythms, such as congenital long QT syndrome;
• Patients who take medications, such as diuretics, which may cause electrolyte abnormalities;
• Patients with hypokalemia or hypomagnesemia.
Ondansetron injection should be avoided in these patients, since they may be more at risk for cardiac arrhythmias, such as QT prolongation and Torsade de Pointes [see Warnings and Precautions (5.2)].

Drug Interactions

• Instruct the patient to report the use of all medications, especially apomorphine, to their healthcare provider. Concomitant use of apomorphine and ondansetron injection may cause a significant drop in blood pressure and loss of consciousness.
• Advise patients of the possibility of serotonin syndrome with concomitant use of ondansetron injection and another serotonergic agent, such as medications to treat depression and migraines. Advise patients to seek immediate medical attention if the following symptoms occur: changes in mental status, autonomic instability, neuromuscular symptoms with or without gastrointestinal symptoms [see Warnings and Precautions (5.3)].

Myocardial Ischemia

Inform patients that ondansetron injection may cause myocardial ischemia during or after the administration. Advise patients to seek immediate medical help if any symptoms suggestive of a myocardial ischemia occur, such as sudden chest pain or chest tightness [see Warnings and Precautions (5.4)].

Masking of Progressive Ileus and Gastric Distension
Inform patients following abdominal surgery or those with chemotherapy-induced nausea and vomiting that ondansetron injection may mask signs and symptoms of bowel obstruction. Instruct patients to immediately report any signs or symptoms consistent with a potential bowel obstruction to their healthcare provider [see Warnings and Precautions (5.5)].

Manufactured by:
Gland Pharma Limited
D.P.Pally, Dundigal Post
Hyderabad – 500 043, India
or
Gland Pharma Limited
Pashamylaram, Patancheru,
Hyderabad – 502 307, India

Manufactured for:
Avet Pharmaceuticals Inc.
East Brunswick, NJ 08816
1.866.901.DRUG (3784)

Revised:09/2025

PACKAGE LABEL.PRINCIPAL DISPLAY PANEL - 4 mg/2 mL

Vial Label:

NDC 23155-547-31 Rx only
Ondansetron
Injection, USP
4 mg/2 mL
(2 mg/mL)
For Intravenous or Intramuscular
Injection

Carton Label:

NDC 23155-547-42 Rx only

Ondansetron
Injection, USP
4 mg/2 mL
(2 mg/mL)
For Intravenous or Intramuscular Injection

PACKAGE LABEL.PRINCIPAL DISPLAY PANEL - 40 mg/20 mL

Vial Label:
NDC 23155-549-31 Rx only
Ondansetron
Injection, USP
40 mg/20 mL
(2 mg/mL)
For Intravenous or Intramuscular
Injection

Carton Label:
NDC 23155-549-31 Rx only
Ondansetron
Injection, USP
40 mg/20 mL
(2 mg/mL)
For Intravenous or
Intramuscular Injection